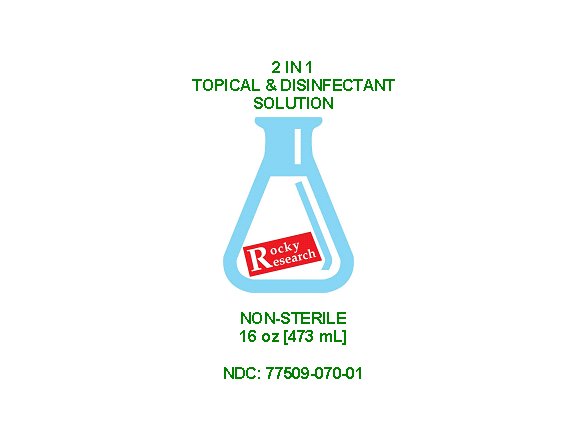 DRUG LABEL: 2 in 1 Hand Sanitizer/Disinfectant
NDC: 77509-070 | Form: LIQUID
Manufacturer: Rocky Research
Category: otc | Type: HUMAN OTC DRUG LABEL
Date: 20200528

ACTIVE INGREDIENTS: ISOPROPYL ALCOHOL 70 mL/100 mL
INACTIVE INGREDIENTS: ALOE VERA LEAF; GLYCERIN 1.5 mL/100 mL; HYDROGEN PEROXIDE 0.126 mL/100 mL; WATER

2 in1 Hand Sanitizer/Disinfectant

The hand sanitizer is manufactured using only the following United States Pharmacopoeia (USP) grade ingredients or higher in the preparation of the product (percentage in final product formulation) consistent with World Health Organization (WHO) recommendations with slight concentration modifications:

1. Isopropyl Alcohol (70%, v/v) in an aqueous solution denatured according to Alcohol and Tobacco Tax and Trade Bureau regulations in 27 CFR part 20.
2. Glycerol (1.5% v/v).
3. Hydrogen peroxide (0.126% v/v).
4. Distilled water.
5. Aloe.
6. Essential oil.

Active Ingredient(s)

Isopropyl Alcohol 70% v/v. Purpose: Antiseptic

Purpose

Antiseptic, Hand Sanitizer & Surface Disinfectant

Use

Hand Sanitize and surface disinfectantr to help reduce bacteria that potentially can cause disease. For use when soap and water are not available.

Warnings

For external use only. Flammable. Keep away from heat or flame

Do not use

- in children less than 2 months of age
- on open skin wounds

When using this product keep out of eyes, ears, and mouth. In case of contact with eyes, rinse eyes thoroughly with water.
Stop use and ask a doctor if irritation or rash occurs. These may be signs of a serious condition.
Keep out of reach of children. If swallowed, get medical help or contact a Poison Control Center right away.

Stop use and ask a doctor if irritation or rash occurs. These may be signs of a serious condition.

Keep out of reach of children. If swallowed, get medical help or contact a Poison Control Center right away.

Directions

- Hands: Spray product in your palm. Rub hands together until dry.
- Surface: Spray product 6-8 inches from surface until thoroughly wet. Wait about 10 seconds then wipe dry. Do not air dry.
- Supervise children under 6 years of age when using this product to avoid swallowing.

Other information

- Store between 15-30C (59-86F)
- Avoid freezing and excessive heat above 40C (104F)
- May cause surface paint or fabric discoloration

Inactive ingredients

glycerin, hydrogen peroxide, distilled water, aloe, essential oil

Package Label - Principal Display Panel

473 ml NDC: 77509-070-01